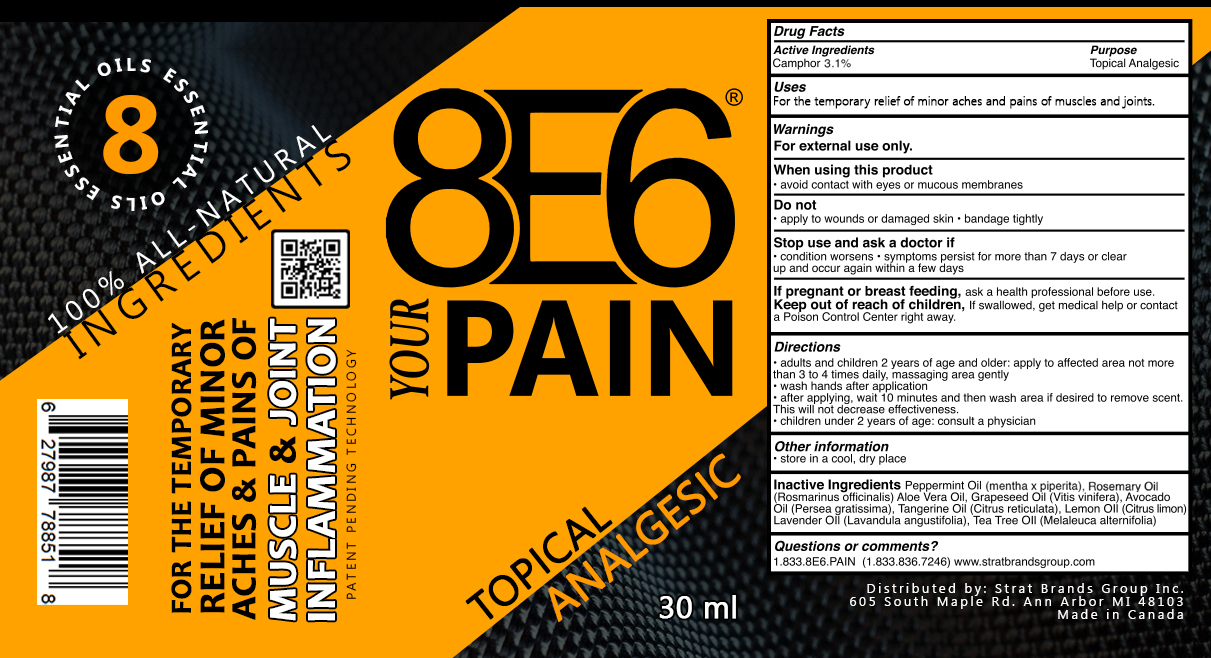 DRUG LABEL: Camphor
NDC: 82600-220 | Form: GEL
Manufacturer: 8E6 YOUR PAIN
Category: otc | Type: HUMAN OTC DRUG LABEL
Date: 20240102

ACTIVE INGREDIENTS: CAMPHOR (NATURAL) 3.1 mg/1 g
INACTIVE INGREDIENTS: PEPPERMINT OIL; AVOCADO OIL; TEA TREE OIL; ALOE VERA LEAF; GRAPE SEED OIL; MANDARIN OIL; ROSEMARY OIL; LEMON OIL; LAVENDER OIL

8E6 YOUR PAIN

ACTIVE INGREDIENT

CAMPHOR 3.1%

PURPOSE

TOPICAL ANALGESIC

WARNINGS

FOR EXTERNAL USE ONLY

WHEN USING THIS PRODUCT

AVOID CONTACT WITH EYES OR MUCOUS MEMBRANES

DO NOT

APPLY TO WOUNDS OR DAMAGED SKIN

BANDAGE TIGHTLY

STOP USE AND ASK A DOCOT IF

CONDITION WORSENS

SYMPTOMS PERSIST FOR MORE THAN 7 DAYS OR CLEAR UP AND OCCUR AGAIN WITHIN A FEW DAYS

IF PREGNANT OR BREAST FEEDING

ASK A HEALTH PROFESSIONAL BEFORE USE

KEEP OUT OF REACH OF CHILDREN

IF SWALLOWED, GET MEDICAL HELP OR CONTACT A POISON CONTROL CENTER RIGHT AWAY

DIRECTIONS

ADULTS AND CHILDREN 2 YEARS OF AGE AND OLDER: APPLY TO AFFECTED AREA NOT MORE THAN 3 TO 4 TIMES DAILY, MASSAGING AREA GENTLY

WASH HANDS AFTER APPLICATION

AFTER APPLYING, WAIT 10 MINUTES AND THEN WASH AREA IF DESIRED TO REMOVE SCENT. THIS WILL NOT DECREASE EFFECTIVENESS

CHILDREN UNDER 2 YEARS OF AGE: CONSULT A PHYSICIAN

OTHER INFORMATION

STORE IN A COOL, DRY PLACE

INACTIVE INGREDIENTS

PEPPERMINT OIL(MENTHA X PIPERITA), ROSEMARY OIL (ROSMARINUS OFFICINALIS), ALOE VERA OIL, GRAPESEED OIL (VITIS VINIFERA), AVOCADO OIL (PERSEA GRATISSIMA), TANGERINE OIL (CITRUS RETICULATA), LEMON OIL (CITRUS LIMON), LAVANDER OIL (LAVANDULA ANGUSTIFOLIA), TRA TREE OIL (MELALEUCA ALTERNIFOLIA)

QUESTIONS OR COMMENTS?

1.833.8E6.PAIN (1.833.836.7246) WWW.STRATBRANDSGROUP.COM

USES

FOR THE TEMPORARY RELIEF OF MINOR ACHES AND PAINS OF MUSCLES AND JOINTS.

8E6 YOUR PAIN

TOPICAL ANALGESIC

30 ML

8 ESSENTIAL OILS

100% ALL-NATURAL INGREDIENTS

FOR THE TEMPORARY RELIEF OF MINOR ACHES & PAINS OF MUSCLE & JOINT INFLAMMATION